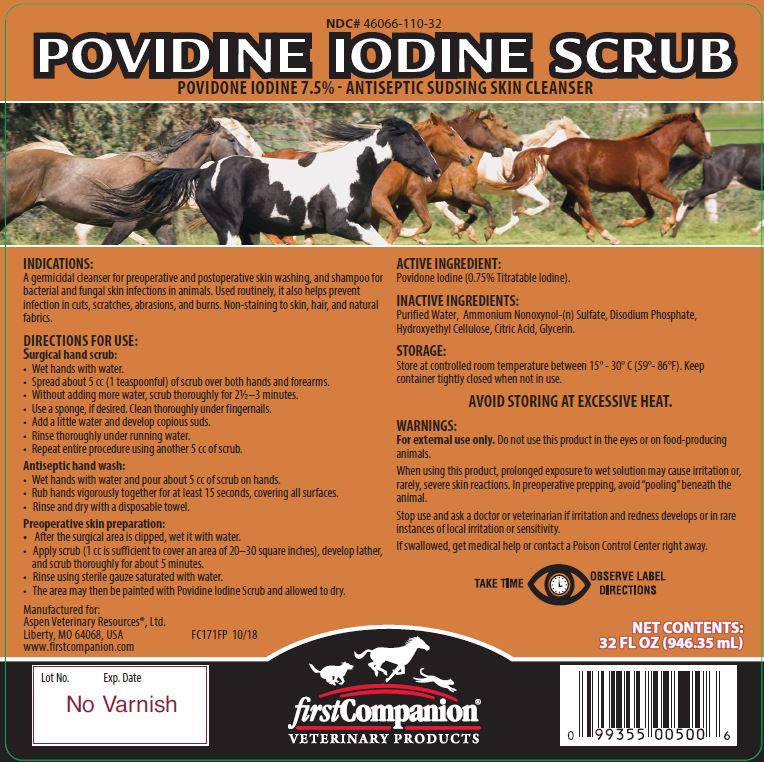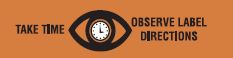 DRUG LABEL: POVIDINE IODINE SCRUB
NDC: 46066-110 | Form: LIQUID
Manufacturer: Aspen Veterinary
Category: animal | Type: OTC ANIMAL DRUG LABEL
Date: 20191030

ACTIVE INGREDIENTS: POVIDONE-IODINE 5.1 g/1 L

POVIDINE IODINE SCRUB

PURPOSE

POVIDONE IODINE 7.5% - ANTISEPTIC SUDSING SKIN CLEANSER

INDICATIONS:

A germicidal cleanser for preoperative and postoperative skin washing, and shampoo for bacterial and fungal skin infections in animals. Used routinely, it also helps prevent infection in cuts, scratches, abrasions, and burns. Non-staining to skin, hair, and natural fabrics.

DIRECTIONS FOR USE:

Surgical hand scrub:

- Wet hands with water.
- Spread about 5 cc (1 teaspoonful) of scrub over both hands and forearms.
- Without adding more water, scrub thoroughly for 2½ –3 minutes.
- Use a sponge, if desired. Clean thoroughly under fingernails.
- Add a little water and develop copious suds.
- Rinse thoroughly under running water.
- Repeat entire procedure using another 5 cc of scrub.

Antiseptic hand wash:

- Wet hands with water and pour about 5 cc of scrub on hands.
- Rub hands vigorously together for at least 15 seconds, covering all surfaces.
- Rinse and dry with a disposable towel.

Preoperative skin preparation:

- After the surgical area is clipped, wet it with water.
- Apply scrub (1 cc is sufficient to cover an area of 20–30 square inches), develop lather, and scrub thoroughly for about 5 minutes.
- Rinse using sterile gauze saturated with water.
- The area may then be painted with Povidine Iodine Scrub and allowed to dry.

ACTIVE INGREDIENT:

Povidone Iodine (0.75% Titratable Iodine).

INACTIVE INGREDIENTS:

Purified Water, Ammonium Nonoxynol-(n) Sulfate, Disodium Phosphate, Hydroxyethyl Cellulose, Citric Acid, Glycerin.

STORAGE:

Store at controlled room temperature between 15° - 30° C (59°-86°F). Keep container tightly closed when not in use.
AVOID STORING AT EXCESSIVE HEAT.

WARNINGS:

For external use only. Do not use this product in the eyes or on food-producing animals.

When using this product, prolonged exposure to wet solution may cause irritation or, rarely, severe skin reactions. In preoperative prepping, avoid “pooling” beneath the animal.

Stop use and ask a doctor or veterinarian if irritation and redness develops or in rare instances of local irritation or sensitivity.

If swallowed, get medical help or contact a Poison Control Center right away.

NET CONTENTS:

32 FL OZ (946.35 mL)

INFORMATION FOR OWNERS/CAREGIVERS

Manufactured for:
Aspen Veterinary Resources®, Ltd.
www.f irstcompanion.com
Liberty, MO 64068, USA FC171FP 10/18